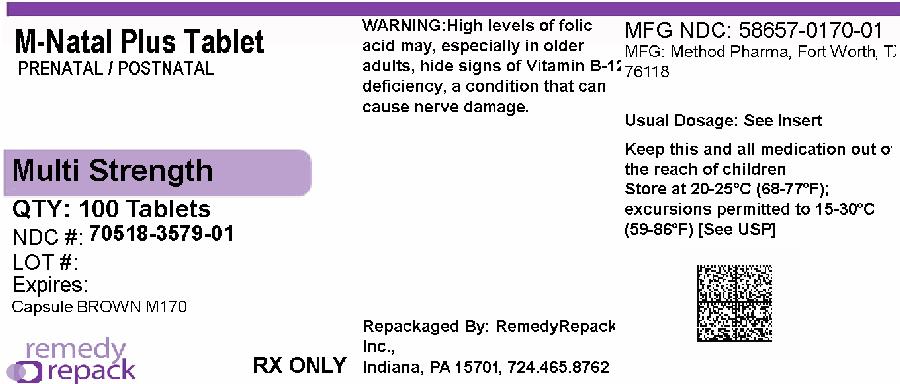 DRUG LABEL: M-Natal Plus
NDC: 70518-3579 | Form: TABLET
Manufacturer: REMEDYREPACK INC.
Category: prescription | Type: HUMAN PRESCRIPTION DRUG LABEL
Date: 20260217

ACTIVE INGREDIENTS: VITAMIN A 4000 [iU]/1 1; ASCORBIC ACID 120 mg/1 1; VITAMIN D 400 [iU]/1 1; .ALPHA.-TOCOPHEROL ACETATE 22 [iU]/1 1; THIAMINE 1.84 mg/1 1; RIBOFLAVIN 3 mg/1 1; NIACIN 20 mg/1 1; PYRIDOXINE HYDROCHLORIDE 10 mg/1 1; FOLIC ACID 1 mg/1 1; CYANOCOBALAMIN 12 ug/1 1; CALCIUM 200 mg/1 1; FERROUS FUMARATE 27 mg/1 1; ZINC 25 mg/1 1; COPPER 2 mg/1 1
INACTIVE INGREDIENTS: MICROCRYSTALLINE CELLULOSE; CROSCARMELLOSE SODIUM; POLYVINYL ALCOHOL, UNSPECIFIED; STEARIC ACID; TITANIUM DIOXIDE; POLYETHYLENE GLYCOL, UNSPECIFIED; TALC; MAGNESIUM STEARATE; SILICON DIOXIDE; CARAMEL; CARNAUBA WAX

M-Natal Plus

M-Natal Plus tablet

Supplement Facts
Serving Size: 1 Tablet
 | Amount Per Serving | % Daily Value for Pregnant and Lactating Women
Vitamin A (as Acetate and Beta Carotene) | 4000 IU | 50%
Vitamin C (Ascorbic Acid) | 120 mg | 200%
Vitamin D (Vitamin D3 as cholecalciferol) | 400 IU | 100%
Vitamin E (dl-Alpha Tocopheryl Acetate) | 22 IU | 73%
Thiamine (Vitamin B1 from Thiamine Mononitrate) | 1.84 mg | 108%
Riboflavin (Vitamin B2) | 3 mg | 150%
Niacin (Niacinamide) | 20 mg | 100%
Vitamin B6 (as Pyridoxine HCl) | 10 mg | 400%
Folic Acid | 1 mg | 125%
Vitamin B12 (Cyanocobalamin) | 12 mcg | 150%
Calcium | 200 mg | 15%
Iron (Ferrous Fumarate) | 27 mg | 150%
Zinc (Zinc Oxide) | 25 mg | 167%
Copper (Cupric Oxide) | 2 mg | 100%

Other Ingredients: Microcrystalline Cellulose, Croscarmellose Sodium, Polyvinyl Alcohol, Stearic Acid, Titanium Dioxide, Polyethylene Glycol, Talc, Magnesium Stearate, Silicon Dioxide, Beet Powder, Caramel, Carnauba Wax.

DESCRIPTION

M-Natal Plus Tablet is an orally administered prenatal/postnatal prescription folic acid-containing dietary supplement and should be administered under the supervision of a licensed medical practitioner.

DOSAGE AND ADMINISTRATION

Before, during and/or after pregnancy, one tablet daily, with a meal, or as directed by a licensed healthcare practitioner regardless of lactation status.

WARNING:

Accidental overdose of iron-containing products is a leading cause of fatal poisoning in children under 6. Keep this product out of reach of children. In case of accidental overdose, call a doctor or poison control center immediately.

CAUTION

High levels of folic acid may, especially in older adults, hide signs of Vitamin B-12 deficiency (such as pernicious anemia), a condition that can cause nerve damage.

Store at 15° – 30°C (59° – 86°F). [See USP Controlled Room Temperature.] Protect from light and moisture. Dispense in a tight, light-resistant container. Notice: Contact with moisture may produce surface discoloration or erosion.

Call your licensed medical practitioner about side effects. You may report side effects by calling Method at 1-877-250-3427 or FDA at 1-800-FDA-1088.

Supplied as beige tablet, imprinted "M170" dispensed in

NDC: 70518-3579-00

NDC: 70518-3579-01

PACKAGING: 30 in 1 BLISTER PACK

PACKAGING: 100 in 1 BOTTLE PLASTIC

High levels of folic acid may, especially in older adults, hide signs of Vitamin B-12 deficiency (such as pernicious anemia), a condition that can cause nerve damage.

Store at 15° – 30°C (59° – 86°F). [See USP Controlled Room Temperature.] Protect from light and moisture. Dispense in a tight, light-resistant container. Notice: Contact with moisture may produce surface discoloration or erosion.

Repackaged and Distributed By:

Remedy Repack, Inc.

625 Kolter Dr. Suite #4 Indiana, PA 1-724-465-8762

PACKAGE LABEL

DRUG: M-Natal Plus

GENERIC: Vitamin A, Vitamin C, Vitamin D, Vitamin E, Thiamine, Riboflavin, Niacin, Vitamin B6, Folic Acid, Vitamin B12, Calcium, Iron, Zinc, Copper

DOSAGE: TABLET

ADMINSTRATION: ORAL

NDC: 70518-3579-0

NDC: 70518-3579-1

COLOR: brown

SHAPE: RECTANGLE

SCORE: No score

SIZE: 19 mm

IMPRINT: M170

PACKAGING: 30 in 1 BLISTER PACK

PACKAGING: 100 in 1 BOTTLE PLASTIC

ACTIVE INGREDIENT(S):

- VITAMIN A 4000[iU] in 1
- ASCORBIC ACID 120mg in 1
- VITAMIN D 400[iU] in 1
- .ALPHA.-TOCOPHEROL ACETATE 22[iU] in 1
- THIAMINE 1.84mg in 1
- RIBOFLAVIN 3mg in 1
- NIACIN 20mg in 1
- PYRIDOXINE HYDROCHLORIDE 10mg in 1
- FOLIC ACID 1mg in 1
- CYANOCOBALAMIN 12ug in 1
- CALCIUM 200mg in 1
- FERROUS FUMARATE 27mg in 1
- ZINC 25mg in 1
- COPPER 2mg in 1

INACTIVE INGREDIENT(S):

- MICROCRYSTALLINE CELLULOSE
- CROSCARMELLOSE SODIUM
- POLYVINYL ALCOHOL, UNSPECIFIED
- STEARIC ACID
- TITANIUM DIOXIDE
- POLYETHYLENE GLYCOL, UNSPECIFIED
- TALC
- MAGNESIUM STEARATE
- SILICON DIOXIDE
- CARAMEL
- CARNAUBA WAX